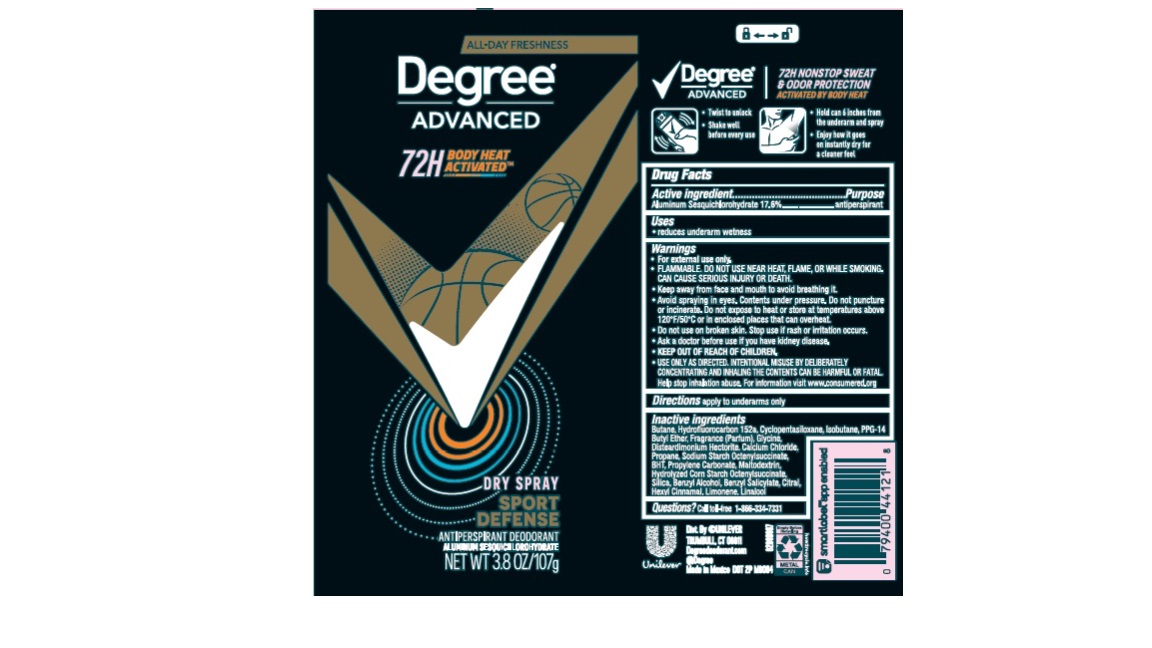 DRUG LABEL: Degree
NDC: 64942-2238 | Form: AEROSOL, SPRAY
Manufacturer: Conopco, Inc. d/b/a Unilever
Category: otc | Type: HUMAN OTC DRUG LABEL
Date: 20241106

ACTIVE INGREDIENTS: ALUMINUM SESQUICHLOROHYDRATE 17.6 g/100 g
INACTIVE INGREDIENTS: BENZYL SALICYLATE; BENZYL ALCOHOL; LINALOOL, (+/-)-; SILICON DIOXIDE; MALTODEXTRIN; PROPYLENE CARBONATE; GLYCINE; LIMONENE, (+)-; ISOBUTANE; CITRAL; BUTANE; 1,1-DIFLUOROETHANE; CYCLOMETHICONE 5; PPG-14 BUTYL ETHER; DISTEARDIMONIUM HECTORITE; CALCIUM CHLORIDE; PROPANE; BUTYLATED HYDROXYTOLUENE; .ALPHA.-HEXYLCINNAMALDEHYDE

Degree Advanced Sport Defense Dry Spray 72H Antiperspirant Deodorant

Drug Facts

Active ingredient

Aluminum Sesquichlorohydrate (17.6%)

Purpose

antiperspirant

Uses

reduces underarm wetness

Directions

For underarms use only

Inactive ingredients

Butane, Hydrofluorocarbon 152a, Cyclopentasiloxane, Isobutane, PPG-14 Butyl Ether, Fragrance (Parfum), Glycine, Disteardimonium Hectorite, Calcium Chloride, Propane, Sodium Starch Octenylsuccinate, BHT, Propylene Carbonate, Maltodextrin, Hydrolyzed Corn Starch Octenylsuccinate, Silica, Benzyl Alcohol, Benzyl Salicylate, Citral, Limonene, Linalool

Questions?

Call toll-free 1-866-334-7331